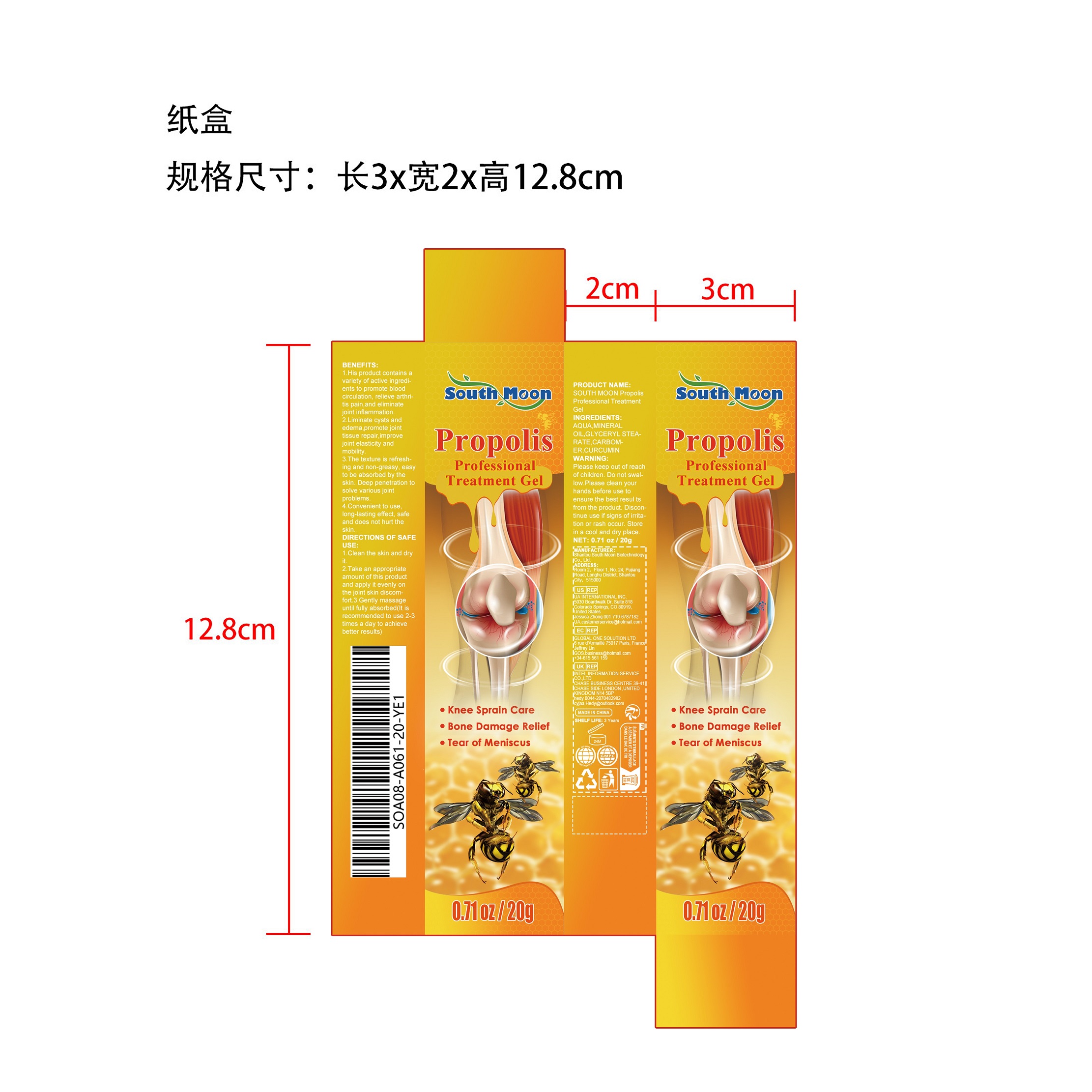 DRUG LABEL: EELHOE Pimple Patches
NDC: 84983-003 | Form: PATCH
Manufacturer: Shantou South Moon Biotechnology Co., Ltd.
Category: otc | Type: HUMAN OTC DRUG LABEL
Date: 20251127

ACTIVE INGREDIENTS: SALICYLIC ACID 2 g/100 g
INACTIVE INGREDIENTS: TEA TREE OIL; CALENDULA OFFICINALIS FLOWER; HYALURONIC ACID; RETINOL

Active ingredients

CURCUMIN 25% w/w

Purpose

Knee Sprain Care

Bone Damage Relief

Tear of Meniscus

Warning

Please keep out of reachof children. Do not swal-low.Please clean yourhands before use toensure the best resul tsfrom the product. Discon-tinue use if signs of irrita-tion or rash occur. Storein a cool and dry place

Please keep out of reachof children.

Directions

1.Clean the skin and dryt.

2.Take an appropriateamount of this productand apply it evenly onthe joint skin discom-fort.

3.Gently massageuntil fully absorbed(lt isrecommended to use 2-3times a day to achievebetter results)

Inactive ingredients

AQUA，MINERALOIL, GLYCERYL MONOSTEARATE， CARBOMER HOMOPOLYMER, UNSPECIFIED TYPE